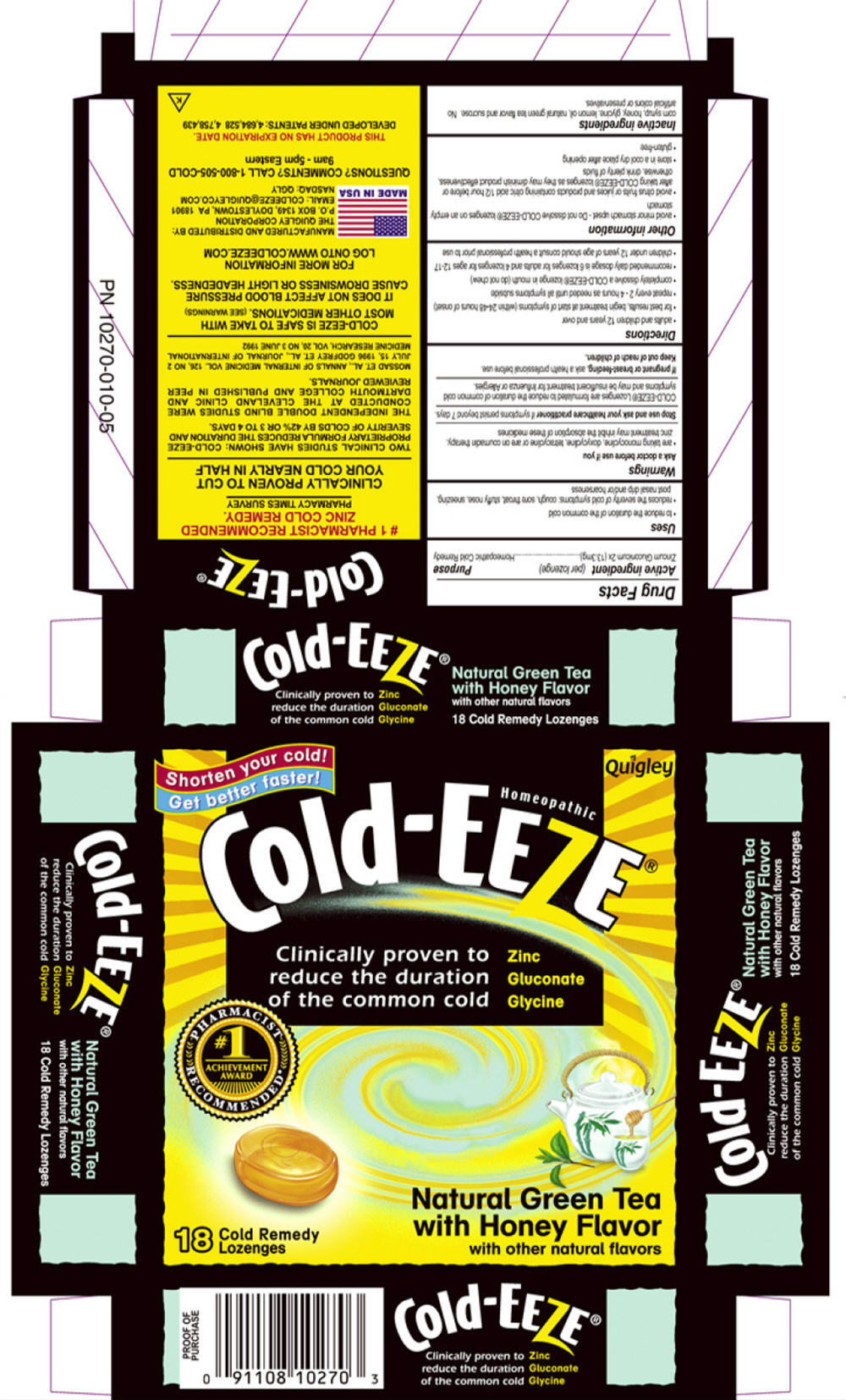 DRUG LABEL: Cold-EEZE 
NDC: 61941-0111 | Form: LOZENGE
Manufacturer: ProPhase Labs, Inc.
Category: homeopathic | Type: HUMAN OTC DRUG LABEL
Date: 20110404

ACTIVE INGREDIENTS: Zinc Gluconate 2 [hp_X]/1 1
INACTIVE INGREDIENTS: Corn Syrup; Glycine; Sucrose

Homeopathic
Cold-EEZE®

Drug Facts

Active ingredient (per lozenge)

Zincum Gluconicum 2x (13.3mg)

Purpose

Homeopathic Cold Remedy

Uses

- to reduce the duration of the common cold
- reduces the severity of cold symptoms: cough, sore throat, stuffy nose, sneezing, post nasal drip and/or hoarseness

Warnings

Ask a doctor before use if you

- are taking monocycline, doxycycline, tetracycline or are on coumadin therapy, zinc treatment may inhibit the absorption of these medicines

Stop use and ask your healthcare practitioner if symptoms persist beyond 7 days.

COLD-EEZE® Lozenges are formulated to reduce the duration of common cold symptoms and may be insufficient treatment for Influenza or Allergies.

PREGNANCY OR BREAST FEEDING

If pregnant or breast-feeding, ask a health professional before use.

Directions

- adults and children 12 years and over
- for best results, begin treatment at start of symptoms (within 24-48 hours of onset)
- repeat every 2 - 4 hours as needed until all symptoms subside
- completely dissolve a COLD-EEZE® lozenge in mouth (do not chew)
- recommended daily dosage is 6 lozenges for adults and 4 lozenges for ages 12-17
- children under 12 years of age should consult a health professional prior to use

Other information

- avoid minor stomach upset - Do not dissolve COLD-EEZE® lozenges on an empty stomach
- avoid citrus fruits or juices and products containing citric acid 1/2 hour before or after taking COLD-EEZE® lozenges as they may diminish product effectiveness, otherwise, drink plenty of fluids

STORAGE AND HANDLING

- store in a cool dry place after opening

- gluten-free

Inactive ingredients

corn syrup, honey, glycine, lemon oil, natural green tea flavor and sucrose. No artificial colors or preservatives.

QUESTIONS? COMMENTS?

CALL 1-800-505-COLD
9am - 5pm Eastern

PRINCIPAL DISPLAY PANEL - 18 Lozenge Carton

Shorten your cold!
Get better faster!

Quigley

Homeopathic
Cold-EEZE®

Clinically proven to
reduce the duration
of the common cold

Zinc
Gluconate
Glycine

PHARMACIST
RECOMMENDED•
#1
ACHIEVEMENT
AWARD

18
Cold Remedy
Lozenges

Natural Green Tea
with Honey Flavor
with other natural flavors